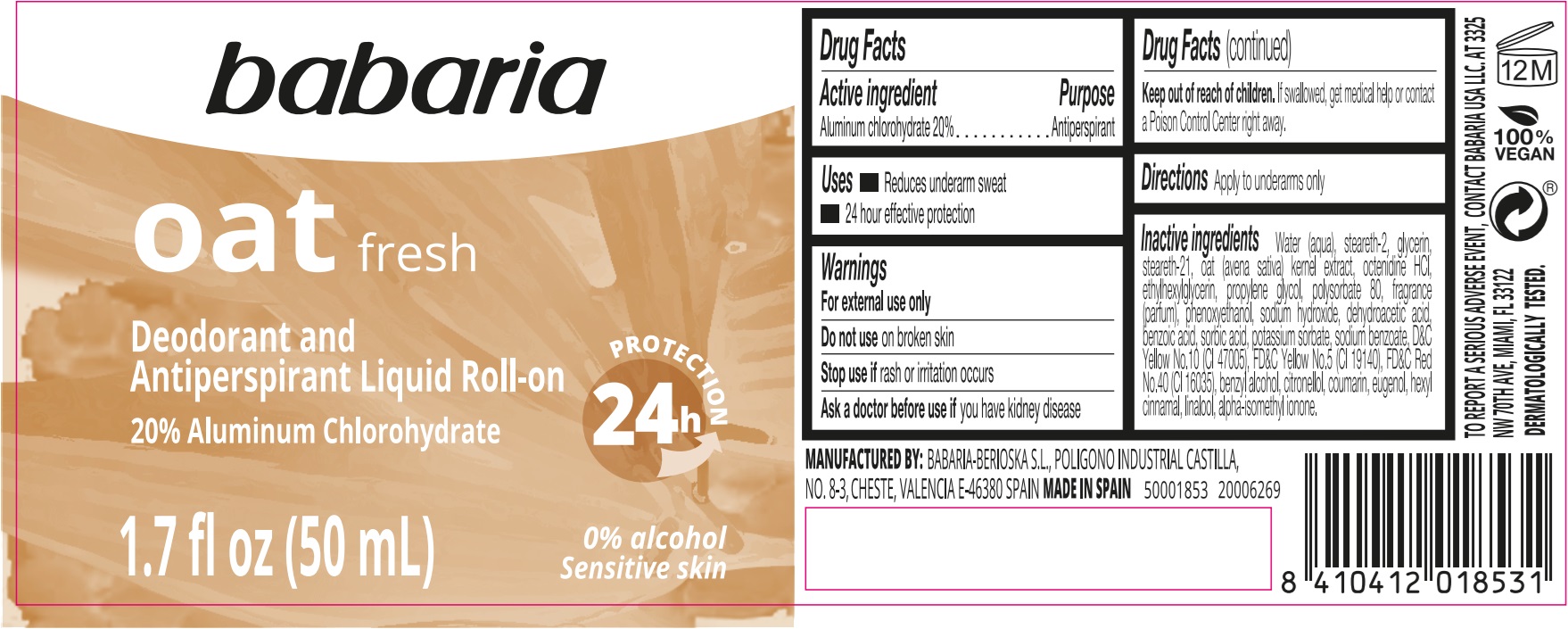 DRUG LABEL: Babaria Oat Fresh Deodorant and Antiperspirant Liquid Roll-On
NDC: 78283-005 | Form: EMULSION
Manufacturer: BERIOSKA SL
Category: otc | Type: HUMAN OTC DRUG LABEL
Date: 20251220

ACTIVE INGREDIENTS: ALUMINUM CHLOROHYDRATE 200 mg/1 mL
INACTIVE INGREDIENTS: WATER; STEARETH-2; GLYCERIN; STEARETH-21; AVENA SATIVA FLOWERING TOP; OCTENIDINE HYDROCHLORIDE; ETHYLHEXYLGLYCERIN; PROPYLENE GLYCOL; POLYSORBATE 80; PHENOXYETHANOL; SODIUM HYDROXIDE; DEHYDROACETIC ACID; BENZOIC ACID; SORBIC ACID; POTASSIUM SORBATE; SODIUM BENZOATE; D&C YELLOW NO. 10; FD&C YELLOW NO. 5; FD&C RED NO. 40; BENZYL ALCOHOL; .BETA.-CITRONELLOL, (R)-; COUMARIN; EUGENOL; .ALPHA.-HEXYLCINNAMALDEHYDE; LINALOOL, (+/-)-; ISOMETHYL-.ALPHA.-IONONE

Babaria Oat Fresh Deodorant and Antiperspirant Liquid Roll-On

Active ingredient

Aluminum chlorohydrate 20%

Purpose

Antiperspirant

Uses

- Reduces underarm sweat
- 24 hour effective protection

Warnings

For external use only

Do not use

on broken skin

Stop use if

rash or irritation occurs

Ask a doctor before use if

you have kidney disease

Keep out of reach of children.

If swallowed, get medical help or contact a Posion Control Center right away.

Directions

Apply to underarms only

Inactive ingredients

Water (aqua), steareth-2, glycerin, steareth-21, oat (avena sativa) kernel extract, octenidine HCL, ethylhexylglycerin, propylene glycol, Polysorbate 80, fragrance (parfum), phenoxyethanol, sodium hydroxide, dehydroacetic acid, benzoic acid, sorbic acid, potassium sorbate, sodium benzoate, D&C Yellow No.10 (CI 47005), FD&C Yellow No.5 (CI 19140), FD&C Red No.40 (CI 16035), benzyl alcohol, citronellol, coumarin, eugenol, hexyl cinnamal, linalool, alpha-isomethyl ionone.